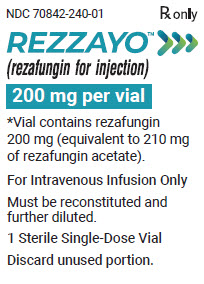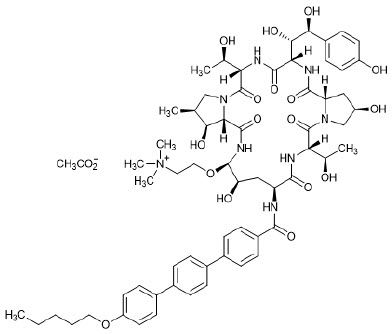 DRUG LABEL: REZZAYO
NDC: 70842-240 | Form: INJECTION, POWDER, LYOPHILIZED, FOR SOLUTION
Manufacturer: Melinta Therapeutics, LLC
Category: prescription | Type: HUMAN PRESCRIPTION DRUG LABEL
Date: 20251223

ACTIVE INGREDIENTS: REZAFUNGIN 200 mg/1 1
INACTIVE INGREDIENTS: MANNITOL; POLYSORBATE 80; HISTIDINE; HYDROCHLORIC ACID; SODIUM CHLORIDE

HIGHLIGHTS OF PRESCRIBING INFORMATION

These highlights do not include all the information needed to use REZZAYO safely and effectively. See full prescribing information for REZZAYO.
REZZAYO® (rezafungin for injection), for intravenous use
Initial U.S. Approval: 2023

RECENT MAJOR CHANGES

Warnings and Precautions, Hypersensitivity Reactions, including Anaphylaxis (5.1) 12/2025

1 INDICATIONS AND USAGE

REZZAYO is an echinocandin antifungal indicated in patients 18 years of age or older who have limited or no alternative options for the treatment of candidemia and invasive candidiasis. Approval of this indication is based on limited clinical safety and efficacy data for REZZAYO. (1, 12.4, 14)

Limitations of Use
REZZAYO has not been studied in patients with endocarditis, osteomyelitis, and meningitis due to Candida. (1)

2 DOSAGE AND ADMINISTRATION

- Administer the recommended dosage of REZZAYO once weekly by intravenous (IV) infusion, with an initial 400 mg loading dose, followed by a 200 mg dose once weekly thereafter. The safety of REZZAYO has not been established beyond 4 weekly doses. (2.1)
- See full prescribing information for reconstitution, dilution, and administration instructions. (2.2, 2.3, 2.4)

3 DOSAGE FORMS AND STRENGTHS

For injection: 200 mg as a solid (cake or powder) in a single-dose vial for reconstitution. (3)

4 CONTRAINDICATIONS

Known hypersensitivity to rezafungin or other echinocandins. (4)

5 WARNINGS AND PRECAUTIONS

- Hypersensitivity Reactions, including Anaphylaxis: Cases of serious hypersensitivity reactions, including anaphylaxis, have been reported in patients receiving REZZAYO. If these reactions occur, discontinue REZZAYO and administer appropriate treatment (5.1).
- Infusion-related Reactions: REZZAYO may cause infusion-related reactions, including flushing, sensation of warmth, urticaria, nausea, or chest tightness. If these reactions occur, slow or pause the infusion. (5.2)
- Photosensitivity: REZZAYO may cause photosensitivity. Advise patients to use protection from sun exposure and other sources of UV radiation. (5.3)
- Hepatic Adverse Reactions: Abnormalities in liver tests have been seen in clinical trial patients treated with REZZAYO. Monitor patients who develop abnormal liver tests and evaluate patients for their risk/benefit of continuing REZZAYO therapy. (5.4)

6 ADVERSE REACTIONS

Most common adverse reactions (incidence ≥ 5%) are hypokalemia, pyrexia, diarrhea, anemia, vomiting, nausea, hypomagnesemia, abdominal pain, constipation, and hypophosphatemia. (6)

To report SUSPECTED ADVERSE REACTIONS, contact Melinta Therapeutics at 1-844-633-6568 or FDA at 1-800-FDA-1088 or www.fda.gov/medwatch.

FULL PRESCRIBING INFORMATION

1 INDICATIONS AND USAGE

1.1 Indication

REZZAYO is indicated in patients 18 years of age or older who have limited or no alternative options for the treatment of candidemia and invasive candidiasis [see Microbiology (12.4)]. Approval of this indication is based on limited clinical safety and efficacy data for REZZAYO [see Clinical Studies (14)].

Limitations of Use
REZZAYO has not been studied in patients with endocarditis, osteomyelitis, and meningitis due to Candida.

1.2 Usage

Specimens for culture and other laboratory data (e.g., histopathology, non-culture diagnostics) should be obtained prior to initiating antifungal therapy. Therapy may be initiated before the results of the cultures and other laboratory tests are known. However, once these results become available, antifungal therapy should be adjusted accordingly.

2 DOSAGE AND ADMINISTRATION

2.1 Recommended Dosage

Administer the recommended dosage of REZZAYO once weekly by intravenous (IV) infusion, with an initial 400 mg loading dose, followed by a 200 mg dose once weekly thereafter. The safety of REZZAYO has not been established beyond 4 weekly doses [see Adverse Reactions (6.1)]. REZZAYO is for intravenous infusion only [see Dosage and Administration (2.4)].

2.2 Missed Doses

If a scheduled dose is missed (not taken on the assigned day), administer the missed dose as soon as possible.

- If the missed dose is administered within 3 days of the assigned day, the next weekly dose may be given on schedule.
- If the missed dose is administered more than 3 days after the assigned day, revise the dosing schedule to ensure there are at least 4 days before the next dose.
- If restarting after at least 2 weeks of missed dosing, the dosing should be started again at the 400 mg loading dose.

2.3 Preparation and Administration of REZZAYO

Reconstitution

REZZAYO is supplied as a single-dose vial containing 200 mg of rezafungin.

For the 400 mg dose, aseptically reconstitute two vials each with 9.5 mL of sterile Water for Injection, to provide a concentration of 20 mg/mL in each vial.

For the 200 mg dose, aseptically reconstitute one vial with 9.5 mL of sterile Water for Injection, to provide a concentration of 20 mg/mL.

Swirl gently to dissolve the white to pale yellow cake or powder. Avoid shaking to minimize foaming. The solution should be clear to pale yellow after dissolution. Parenteral drug products should be inspected visually for particulate matter and discoloration prior to administration, whenever solution and container permit. Do not use if the reconstituted solution is cloudy or has precipitated. The reconstituted solution is not for direct injection and must be diluted before intravenous infusion.

Storage of the Reconstituted Solution

REZZAYO reconstituted solution can be stored between 5°C to 25°C (41°F to 77°F). Stability of the reconstituted solution has been demonstrated for 24 hours when stored at 5°C to 25°C (41°F to 77°F).

Preparation of Intravenous Infusion Solution

See Table 1 for the dilution requirements for infusion solution. First, aseptically withdraw and discard the appropriate volume of diluent from the intravenous bag containing 250 mL of 0.9% Sodium Chloride Injection, 0.45% Sodium Chloride Injection, or 5% Dextrose Injection. Next, aseptically transfer the indicated volume of reconstituted solution (10 mL per vial) into the intravenous bag.

REZZAYO vials are single-dose vials. Discard any unused portion.

Table 1: Dilution Requirements for REZZAYO Prior to Administration
Dose | Number of 200 mg Vials Required | Total Reconstituted Volume Required | Infusion Diluent Volume Discarded | Infusion Diluent Volume Used | Total Infusion Volume
400 mg | 2 | 20 mL | 20 mL | 230 mL | 250 mL [Infusion solution concentration for the 400 mg dose = 1.6 mg/mL]
200 mg | 1 | 10 mL | 10 mL | 240 mL | 250 mL [Infusion solution concentration for the 200 mg dose = 0.8 mg/mL]

Storage of the Intravenous Infusion Solution

Store REZZAYO infusion solution between 5°C to 25°C (41°F to 77°F). Stability of the infusion solution has been demonstrated for 48 hours at 5°C to 25°C (41°F to 77°F).

The infusion solution must not be frozen.

2.4 Administration of Intravenous Infusion Solution

Administer REZZAYO by intravenous infusion over approximately one hour (~250 mL/h). If infusion-related reactions occur, the infusion may be slowed, or paused and restarted at a lower rate [see Warnings and Precautions (5.1)].

3 DOSAGE FORMS AND STRENGTHS

For injection: 200 mg of rezafungin as a sterile white to pale yellow solid (cake or powder) for reconstitution in a single-dose glass vial.

4 CONTRAINDICATIONS

REZZAYO is contraindicated in patients with known hypersensitivity to rezafungin or other echinocandins.

5 WARNINGS AND PRECAUTIONS

5.1 Hypersensitivity Reactions, including Anaphylaxis

Cases of serious hypersensitivity reactions, including anaphylaxis, have been reported in patients receiving REZZAYO. If these reactions occur, discontinue REZZAYO and administer appropriate treatment [see Adverse Reactions (6.2)].

5.2 Infusion-Related Reactions

Infusion-related reactions, including flushing, sensation of warmth, urticaria, nausea, and chest tightness have been observed in clinical trials with REZZAYO. If these reactions occur, slow or pause the infusion and restart at a lower rate [see Dosage and Administration (2.4)].

5.3 Photosensitivity

REZZAYO may cause photosensitivity. Patients should be advised to use protection from sun exposure and other sources of UV radiation during REZZAYO treatment.

5.4 Hepatic Adverse Reactions

Abnormalities in liver tests have been seen in clinical trial patients treated with REZZAYO [see Adverse Reactions (6.1)]. In some patients with serious underlying medical conditions who were receiving multiple concomitant medications along with REZZAYO, clinically significant hepatic abnormalities have occurred. Monitor patients who develop abnormal liver tests during REZZAYO therapy and evaluate patients for their risk/benefit of continuing REZZAYO therapy.

6 ADVERSE REACTIONS

The following clinically significant adverse reactions are described elsewhere in the labeling:

- Hypersensitivity Reactions, including Anaphylaxis [see Warnings and Precautions (5.1)]
- Infusion-related Reactions [see Warnings and Precautions (5.2)]
- Hepatic Adverse Reactions [see Warnings and Precautions (5.4)]

6.1 Clinical Trials Experience

Because clinical trials are conducted under widely varying conditions, adverse reaction rates observed in the clinical trials of REZZAYO cannot be directly compared to rates in the clinical trials of another drug and may not reflect the rates observed in practice.

The safety of REZZAYO was assessed in 76 subjects in phase 1 studies and 232 patients with candidemia and invasive candidiasis in Trials 1 and 2, who received a 400 mg loading dose followed by a 200 mg dose once weekly or higher (please note that after the loading dose of 400 mg, weekly doses higher than 200 mg are not approved). A total of 151 patients received an initial 400 mg loading dose followed by a 200 mg dose once weekly thereafter (400 mg/200 mg dose); the maximum duration of dosing was 4 weekly doses (including the loading dose).

In the pooled Trial 1 and 2 safety database of REZZAYO patients treated with the 400 mg/200 mg dose, the age range was 19-91 years, the gender distribution was 64.9% male and 35.1% females, and the race distribution was 66.2% White, 7.9% Black, 17.9% Asian, 2.7% other, and 5.3% not reported.

Adverse Reactions Leading to Discontinuation in Patients with Candidemia and Invasive Candidiasis

The number of patients with an adverse reaction leading to discontinuation of study medication was 9.3% in the REZZAYO arm and 9.0% in the caspofungin arm. In Trial 2, patients with a history (or presenting with significant symptoms) of severe ataxia, tremor, or neuropathy or a diagnosis of multiple sclerosis or a movement disorder (including Parkinson's Disease or Huntington's Disease) or currently taking a known neurotoxic medication were excluded from the trial.

Most Common Adverse Reactions in Patients with Candidemia and Invasive Candidiasis

Selected adverse reactions occurring in 5% or more of the patients, who received a 400 mg loading dose followed by a 200 mg dose of REZZAYO once weekly are shown in Table 2.

Table 2: Adverse Reactions Reported in ≥5% of Adult Patients Receiving REZZAYO Therapy for Candidemia/Invasive Candidiasis
Adverse Reaction | REZZAYO N = 151 n (%) | Caspofungin N = 166 n (%)
Gastrointestinal disorders
Diarrhea | 17 (11%) | 17 (10%)
Vomiting | 14 (9%) | 7 (4%)
Nausea | 13 (9%) | 8 (5%)
Abdominal pain | 11 (7%) | 9 (5%)
Constipation | 8 (5%) | 8 (5%)
Metabolism and nutrition disorders
Hypokalemia | 22 (15%) | 17 (10%)
Hypomagnesemia | 12 (8%) | 5 (3%)
Hypophosphatemia | 8 (5%) | 5 (3%)
General disorders
Pyrexia | 18 (12%) | 11 (7%)
Blood and lymphatic system disorders
Anemia | 15 (10%) | 13 (8%)

Less Common Adverse Reactions in Patients with Candidemia and Invasive Candidiasis

The following selected adverse reactions occurred in <5% of patients receiving REZZAYO: infusion-related reactions, tremor, disseminated intravascular coagulation, dysphagia, gastrointestinal hemorrhage, fluid overload, insomnia, erythema, headache, dizziness, acute kidney injury, abnormal liver tests (including hypertransaminasemia and increased gamma-glutamyltransferase), peripheral neuropathy (includes neuropathy peripheral, polyneuropathy, and peroneal nerve palsy).

Tremors

Tremors were reported in 4/151 (2.6%) of REZZAYO-treated patients and none of the caspofungin-treated patients in Trials 1 and 2. All tremors developed in the second or third week after initiation of REZZAYO treatment and resolved within a month of onset.

6.2 Postmarketing Experience

The following adverse reactions have been identified during post approval use of REZZAYO. Because these reactions are reported voluntarily from a population of uncertain size, it is not always possible to reliably estimate their frequency or establish a causal relationship to drug exposure.

Immune system disorders: drug hypersensitivity, anaphylactic reaction

8 USE IN SPECIFIC POPULATIONS

8.1 Pregnancy

Risk Summary

There are no data on the use of REZZAYO during pregnancy to evaluate for a drug-associated risk of major birth defects, miscarriage, or other adverse maternal or fetal outcomes. No adverse embryofetal outcomes were observed when rezafungin was dosed intravenously to pregnant rats or rabbits during the period of organogenesis up to approximately 5 or 3 times the clinical exposure based on AUC comparison (see Data). In a pre- and post- natal study, there were no adverse effects on offspring growth, maturation, or measures of neurobehavioral or reproductive function in rats at doses up to about 5 times the recommended human dose based on AUC comparisons.

The background risk of major birth defects and miscarriage for the indicated population is unknown. All pregnancies have a background risk of birth defect, loss, or other adverse outcomes. In the U.S. general population, the estimated background risk of major birth defects and miscarriage in clinically recognized pregnancies is 2% to 4% and 15% to 20%, respectively.

Data

Animal Data

In an embryofetal development study, intravenous rezafungin was administered at doses up to 45 mg/kg, once every 3 days to female rats one week prior to pairing with untreated males, and dosing was continued through mating to gestation day 17. Maternal toxicity included a transient histamine-release response (hypoactivity, ataxia, flushed extremities, dilated pupils and/or swollen facial area) at rezafungin doses of 15 mg/kg and above. No adverse embryofetal outcomes were observed in rat pups at rezafungin doses of 45 mg/kg, equivalent to 5 times the clinical exposure based on AUC comparisons.

No adverse outcomes were observed when rezafungin was dosed intravenously once every 3 days to pregnant rabbits during the period of organogenesis (GD 7 to 19) at doses up to 35 mg/kg (approximately 3 times the clinical exposure) despite maternal toxicity (reduced bodyweight gain).

In a pre- and post-natal study, there were no adverse effects on offspring growth, maturation, or measures of neurobehavioral or reproductive function in rats administered rezafungin intravenously once every 3 days from 1 week prior to mating through weaning (LD20), at doses up to 45 mg/kg/day (about 5 times the recommended human dose based on AUC comparisons).

8.2 Lactation

Risk Summary

There are no data on the presence of rezafungin or its metabolite in human milk, the effects on the breastfed infant, or the effects on milk production. Rezafungin was present in rat milk. When a drug is present in animal milk, it is likely that the drug will be present in human milk. The developmental and health benefits of breastfeeding should be considered along with the mother's clinical need for REZZAYO and any potential adverse effects on the breastfed infant from REZZAYO or from the underlying maternal condition.

8.3 Females and Males of Reproductive Potential

Infertility

Males

Based on rat studies, rezafungin could lead to decreased sperm motility, decreased sperm numbers, and increased incidence of sperm with abnormal morphology. The effect of REZZAYO on human fertility is unknown [see Nonclinical Toxicology (13.1)].

8.4 Pediatric Use

The safety and effectiveness of REZZAYO have not been established in pediatric patients.

8.5 Geriatric Use

Of the 151 rezafungin-treated patients at the proposed dose in Trials 1 and 2, 64 patients (42%) were 65 years of age and older, while 26 patients (17%) were 75 years of age and older.

Clinical studies of REZZAYO did not include sufficient numbers of older adult patients to determine if patients 65 years and older respond differently than younger adult patients.

10 OVERDOSAGE

No cases of overdose were reported during the clinical studies. Rezafungin is highly protein bound and not anticipated to be dialyzable.

11 DESCRIPTION

REZZAYO (rezafungin for injection), for intravenous use is a sterile solid (cake or powder) that contains rezafungin acetate. Rezafungin acetate is a semisynthetic lipopeptide synthesized from a fermentation product of Aspergillus nidulans. REZZAYO is an echinocandin, a class of antifungal drugs that inhibits the synthesis of 1,3-β-D-glucan, an essential component of fungal cell walls.

REZZAYO contains 210 mg of rezafungin acetate, equivalent to 200 mg of rezafungin. REZZAYO also contains 47 mg histidine, 500 mg mannitol, 450 mg polysorbate 80, and hydrochloric acid and/or sodium hydroxide for pH adjustment. Rezafungin acetate is a hygroscopic, white to off-white powder. It is freely soluble in water, soluble in methanol, and sparingly soluble in ethanol.

Rezafungin acetate is chemically designated as Echinocandin B, 1-[(4R,5R)-4-hydroxy-N^2-[[4"- (pentyloxy)[1,1':4',1"-terphenyl]-4-yl]carbonyl]-5-[2-(trimethylammonio)ethoxy]-L-ornithine]-4-[(4S)-4- hydroxy-4-(4-hydroxyphenyl)-L-allothreonine]-, acetate (1:1).

The empirical formula of rezafungin acetate is C63H85N8O17 • C2H3O2, and the formula weight is 1285.46 g/mol.

The chemical structure of rezafungin acetate is:

12 CLINICAL PHARMACOLOGY

12.1 Mechanism of Action

Rezafungin is an echinocandin antifungal drug [see Microbiology (12.4)].

12.2 Pharmacodynamics

Rezafungin exposures achieved with the recommended dosage regimen appear to be on the plateau of the observed flat exposure-efficacy response curve in clinical studies.

Cardiac Electrophysiology

Rezafungin does not prolong the QTc interval to any clinically relevant extent at a dose 3.5 times the maximum approved recommended loading dose.

12.3 Pharmacokinetics

Following single and multiple dosing, the Cmax and AUC of rezafungin increase in a dose-proportional manner over a dose range of 50 mg (0.125 times the approved maximum recommended loading dose) to 400 mg.

Rezafungin population PK model derived pharmacokinetics (in patients with candidemia and invasive candidiasis (IC)) following administration of REZZAYO are provided in Table 3 and presented as mean ± standard deviation (SD). The mean rezafungin AUC0-168h decreased approximately 30% and Cmax decreased approximately 19% in patients with candidemia and IC compared to healthy participants.

Table 3: Population Pharmacokinetic (PK) Parameters of Rezafungin in Patients with Candidemia or IC Following REZZAYO (initial 400 mg loading dose, followed by a 200 mg dose once weekly).
Parameter | Value [Mean ± SD]
Exposure | Day 1 | Day 15
Cmax(mcg/mL) [Time to Cmax is 1hr post-start of infusion (i.e., end of infusion)] | 19.2 ± 5.9 | 11.8 ± 3.5
AUC0-168 (mcg∙h/mL) | 827 ± 252 | 667 ± 224
Cmin (mcg/mL) | 2.4 ± 0.9 | 2.2 ± 0.9
Distribution
% Bound to human plasma proteins | Mean estimates varied from 87.5% to 93.6% in patients Mean estimates varied from 95.6% to >98.6% in healthy adults
Volume of distribution (V) | 67±28L
Elimination
Clearance (CL) | 0.35 ± 0.13 L/hr
terminal half-life (t1/2) | 152 ± 29 hours
Metabolism
Metabolic pathways | Hepatic metabolism of rezafungin has not been observed. It is unlikely that rezafungin is a clinically relevant substrate of CYP450 enzymes
Excretion [Excretion studied in healthy subjects]
Major route of elimination | Fecal excretion
% feces | 74.3% of recovered radioactivity, primarily as rezafungin
% urine | 25.7% of recovered radioactivity, primarily as inactive metabolites
Cmax= maximum plasma concentration; Cmin= trough plasma concentration; AUC0–168h= area under the plasma concentration-time curve from time zero to 168 hours post dose

Specific Populations

No clinically relevant effects on the pharmacokinetics of rezafungin were observed based on age (range: 20 to 89 years), sex (60.6% male), race (~10% Asian, 10% Black, 77% White), weight (range: 34 to 154.5 kg), or hepatic impairment (Child Pugh Class B or C). No clinically relevant effect on the pharmacokinetics of rezafungin were observed based on renal impairment (creatinine clearance: 9.3 mL/min to above 120 mL/min) and no effect is expected in patients undergoing hemodialysis.

Drug Interaction Studies

Clinical Studies

Drug-drug interaction studies' findings in healthy subjects show that at the recommended rezafungin dosing regimen, no clinically significant effect is expected of rezafungin treatment on the pharmacokinetics of substrates of cytochrome P450 (CYP) enzymes and/or drug transporters (repaglinide [CYP2C8], cyclosporine [CYP3A and P-gp], tacrolimus [CYP3A and P-gp], caffeine [CYP1A2], midazolam [CYP3A]), metformin [OCT-1 and OCT-2 and MATE-1 and MATE-2], pitavastatin [OATP], rosuvastatin [BCRP and OATP], digoxin [P-gp]). These studies also show no clinically significant effect expected of rezafungin treatment on the pharmacokinetics of other drugs likely to be co-administered (ibrutinib, venetoclax, efavirenz, or mycophenolate mofetil).

In Vitro Studies

Rezafungin is not a substrate of CYP enzymes or drug transporter systems. Rezafungin is not an inhibitor or inducer of common drug metabolizing CYP enzymes or transporter systems.

12.4 Microbiology

Mechanism of Action

Rezafungin is a semi-synthetic echinocandin. Rezafungin inhibits the 1,3-β-D-glucan synthase enzyme complex, which is present in fungal cell walls but not in mammalian cells. This results in inhibition of the formation of 1,3-β-D-glucan, an essential component of the fungal cell wall of many fungi, including Candida species (spp.). Inhibition of 1,3-β-D-glucan synthesis results in concentration-dependent in vitro fungicidal activity against Candida spp., however, the clinical significance of this activity is unknown.

Resistance

Reduced susceptibility to echinocandins predominantly arises from mutations in glucan synthase catalytic subunit-encoding FKS genes (FKS1 and/or FKS2) that impact residues comprising "hot spot" (HS) regions of the Fks protein. Rezafungin exhibits some degree of cross-resistance to all fks mutations that confer reduced susceptibility to echinocandins. The relevance of fks-based reduced susceptibility to clinical outcome has not been fully characterized for rezafungin.

Interaction with Other Antimicrobials

In vitro studies have not demonstrated antagonism between rezafungin and azoles, amphotericin B, or flucytosine. In vitro studies have not demonstrated antagonism for rezafungin versus bacteria in combination with the following antibacterial drug classes: aminoglycosides, carbapenems, cephalosporins, fluoroquinolones, glycopeptides, macrolides, monobactams, oxazolidinones, polypeptides, rifamycins, sulfonamides, and tetracyclines, as well as daptomycin.

Antifungal Activity

Rezafungin has been shown to be active against most isolates of the following microorganisms both in vitro and in clinical infections.
Candida albicans
Candida glabrata
Candida parapsilosis
Candida tropicalis

The following in vitro data are available, but their clinical significance is unknown. At least 90 percent of the following fungi exhibit an in vitro minimum inhibitory concentration (MIC) less than or equal to the susceptible breakpoint for rezafungin against isolates of a similar genus or organism group. However, the efficacy of rezafungin in treating clinical infections caused by these fungi has not been established in adequate and well-controlled clinical trials.
Candida krusei
Candida auris
Candida dubliniensis
Candida fabianii
Candida guilliermondii
Candida inconspicua
Candida kefyr
Candida lusitaniae
Candida metapsilosis
Candida orthopsilosis
Candida pulcherrima
Candida rugosa
Candida sojae

Susceptibility Testing

For specific information regarding susceptibility test interpretive criteria and associated test methods and quality control standards recognized by FDA for this drug, please see: https://www.fda.gov/STIC.

13 NONCLINICAL TOXICOLOGY

13.1 Carcinogenesis, Mutagenesis, Impairment of Fertility

Carcinogenesis

Carcinogenicity studies with rezafungin have not been conducted.

Mutagenesis

Rezafungin was negative in a standard battery of assays, including an in vitro bacterial reverse mutation assay, an in vitro mammalian clastogenicity assay, and an in vivo rat bone marrow micronucleus assay.

Impairment of Fertility

Rezafungin did not affect mating or fertility in male and female rats following IV administration once every 3 days at doses up to 45 mg/kg (6 times the clinical exposure, based on AUC determined in a separate rat study). Decreased sperm motility was noted at ≥30 mg/kg and most males at 45 mg/kg showed mild/moderate hypospermia and had no detectable motile sperm. At rezafungin doses ≥30 mg/kg there was an increased incidence of sperm with abnormal morphology as well as mild to moderate degeneration of the seminiferous tubules. In a 3-month study of every 3 day IV rezafungin in rats, males dosed at 45 mg/kg showed minimal tubular degeneration/atrophy in the testes and cellular debris in the epididymides at the end of 3 months. The incidence of this finding reduced by the end of a 4-week reversibility period. In contrast, sperm concentration, production rate, morphology and motility were unaffected in adult monkeys dosed weekly with rezafungin, up to 30 mg/kg (about 6 times the clinical dose based on AUC comparisons) for 11 or 22 weeks or after a 52-week recovery period.

13.2 Animal Toxicology and/or Pharmacology

In one 3-month study in monkeys using every-3-day dosing, tremors were observed, beginning 35 to 43 days after the beginning of dosing at and above 30 mg/kg (9 times the clinical exposure based on AUC comparison). Increased cellularity/hyperplasia of Schwann cells and nerve fiber degeneration (affecting axons and/or myelin) were observed at 30 mg/kg (9 times the clinical exposure based on AUC comparison) and above. Tremors and demyelination persisted in the fourth week of a 4-week reversibility period. A subsequent 26-week monkey study using weekly rezafungin dosing up to 30 mg/kg (6 times the clinical exposure based on AUC comparison) showed a non-dose dependent increase in tremors, axonal degeneration, or demyelination compared to controls beginning at doses similar to human exposures (5 mg/kg). In one animal in the 15 mg/kg cohort (3 times the clinical exposure based on AUC comparison), tremors persisted to the end of the 52-week reversibility period. In rats dosed weekly for 26 weeks, intravenous rezafungin was associated with an increased incidence of axonal/nerve fiber degeneration at 25 and 45 mg/kg (2- and 4-times the clinical dose based on AUC comparison) at the end of the 26-week reversibility period.

Rezafungin induced an acute transient histamine-release response in rats. In monkeys, both the vehicle and rezafungin induced a mild transient histamine-like response in some studies.

14 CLINICAL STUDIES

The safety and efficacy of REZZAYO in the treatment of patients with candidemia and/or invasive candidiasis (IC) were evaluated in a multicenter, randomized, double-blind study (Trial 1; NCT03667690). Patients were randomized in a 1:1 ratio to receive REZZAYO or caspofungin. Randomization was stratified based on diagnosis (candidemia only; IC) and by Acute Physiology and Chronic Health Evaluation II score (APACHE II)/absolute neutrophil count (ANC) at screening. Patients with septic arthritis in a prosthetic joint, osteomyelitis, endocarditis or myocarditis, meningitis, endophthalmitis, chorioretinitis, or any central nervous system infection, chronic disseminated candidiasis, or urinary tract candidiasis due to ascending Candida infection secondary to obstruction or surgical instrumentation of the urinary tract were excluded.

Patients in the REZZAYO arm were to receive a single 400 mg loading dose on Day 1 of Week 1, followed by 200 mg once weekly, for a total of two to four doses. Patients in the caspofungin arm were to receive a single 70 mg IV loading dose, followed by caspofungin 50 mg IV once daily treatment for a total of 2 to 4 weeks. After ≥3 days of IV therapy, patients in the caspofungin group could be switched to oral step-down therapy (fluconazole), if the patient met the criteria for cure and was preparing to be discharged.

One hundred and ninety-nine patients in the intent-to-treat (ITT) population were randomized. The age range was 19-91 years, the gender distribution was 62% male and 38% female, and the race distribution was 61% White, 5% Black, 29% Asian, and 5% other races or not reported. The median duration of therapy was 14 days in the two treatment arms.

The modified ITT (mITT) population included 187 patients with a culture positive for Candida species within 4 days before randomization and who received at least one dose of study drug. The most frequent species isolated at baseline was C. albicans (42%), followed by C. glabrata (26%), C. tropicalis (20%), and C. parapsilosis (13%). The majority (70%) of patients had a diagnosis of candidemia only. The majority (93%) of patients were not neutropenic (ANC ≥500) and 84% had APACHE II scores less than 20. Risk factors for candidemia were: receipt of broad-spectrum antibacterial drugs (71%), presence of a central venous catheter (60%), major surgery (35%), diabetes mellitus (29%), active malignancy (25%), and total parenteral nutrition (20%). Mechanically ventilated patients were 24% (17% and 30% in the REZZAYO and caspofungin group, respectively).

Efficacy was assessed by all-cause mortality at Day 30. The number and percentage of patients in each treatment group who were alive and deceased/unknown survival status at Day 30 was determined in the mITT population. Additional efficacy outcomes were global cure (mycological eradication/presumed eradication, clinical cure, and radiological cure [for patients with documented IC by radiologic or other imaging findings at baseline]), mycological eradication/presumed eradication, and investigator's assessment of clinical cure. Results of the efficacy endpoints are shown in Table 4.

Table 4: Summary of Efficacy Results from Trial 1 (mITT Population)
 | REZZAYO 400 mg/200 mg N = 93 n (%) | Caspofungin 70 mg/50 mg N = 94 n (%) | Difference (95% CI) [Two-sided 95% confidence intervals (CIs) for the observed differences in cure rates (REZZAYO minus caspofungin) is calculated using the unadjusted methodology of Miettinen and Nurminen.]
All-Cause Mortality (Day 30) [Patients who died on or before Day 30, or with unknown survival status.] | 22 (23.7) | 20 (21.3) | 2.4 (-9.7, 14.4)
Global Cure [Patients with a mycological eradication/presumed eradication, clinical cure and radiologic cure (for patients with IC documented by radiologic or other imaging findings at baseline), as adjudicated by the Data Review Committee.]
Day 5 | 52 (55.9) | 49 (52.1) | 3.8 (-10.5, 17.9)
Day 14 | 55 (59.1) | 57 (60.6) | -1.5 (-15.4, 12.5)
Clinical Cure [Investigator's assessment of clinical response based on resolution of attributable systemic signs and symptoms of candidemia/IC, no new systemic signs or symptoms attributable to candidemia/IC, no new systemic antifungal therapy to treat candidemia/IC, and the subject is alive.]
Day 5 | 59 (63.4) | 70 (74.5) | -11.0 (-24.0, 2.3)
Day 14 | 62 (66.7) | 63 (67.0) | -0.4 (-13.8, 13.1)
Day 30 | 51 (54.8) | 52 (55.3) | -0.5 (-14.6, 13.7)
Mycological eradication/presumed eradication [Negative blood culture or culture from a normally sterile site and no change in antifungal therapy for the treatment of candidemia and/or IC. For IC patients, if the normally sterile baseline site of Candida infection was not accessible, the patient was presumed to have an eradication if the clinical outcome and radiologic outcome (if assessed) was a cure.]
Day 5 | 64 (68.8) | 58 (61.7) | 7.1 (-6.6, 20.6)
Day 14 | 63 (67.7) | 62 (66.0) | 1.8 (-11.7, 15.2)

A multicenter, randomized, dose-finding, exploratory, double-blind study was conducted in subjects with candidemia and/or invasive candidiasis (Trial 2: NCT02734862). The primary objectives of this study were to evaluate safety and tolerability of rezafungin and overall success (mycological eradication and resolution of systemic signs attributable to candidemia and/IC) at Day 14. The study provides safety and supportive efficacy data.

16 HOW SUPPLIED/STORAGE AND HANDLING

16.1 How Supplied

REZZAYO (rezafungin for injection) is supplied as sterile white to pale yellow solid (cake or powder) in a single-dose 20 mL Type I glass vial with a stopper, an aluminum seal, and blue polypropylene flip-off cap. The vial stopper is not made with natural rubber latex.

REZZAYO is available in the following packaging configuration:

One single-dose vial of REZZAYO 200 mg (NDC 70842-240-01)

16.2 Storage and Handling

REZZAYO Vials

REZZAYO vials should be stored at 20°C to 25°C (68°F to 77°F). Brief exposure to 15°C to 30°C (59°F to 86°F) permitted [see USP Controlled Room Temperature].

Reconstituted Solution

REZZAYO reconstituted solution can be stored between 5°C (41°F) and 25°C (77°F) for up to 24 hours [see Dosage and Administration (2.3)].

IV Infusion Solution

REZZAYO infusion solution can be stored between 5°C (41°F) and 25°C (77°F) for up to 48 hours. Do not freeze [see Dosage and Administration (2.3)].

17 PATIENT COUNSELING INFORMATION

Serious Allergic Reactions

Advise patients that serious allergic reactions could occur with REZZAYO and that serious reactions require immediate treatment [see Warnings and Precautions (5.1)].

Photosensitivity

Advise patients to use protection against sun exposure and other sources of UV radiation during treatment because REZZAYO may cause photosensitivity [see Warnings and Precautions (5.3)].

Distributed by:
Melinta Therapeutics LLC
Parsippany, NJ 07054
USA

Manufactured by:
Patheon Italia S.p.A., a Thermo Fisher Scientific company
Viale Gian Battista Stucchi 110
20900 Monza (MB)
Italy

MEL150-R001

PACKAGE LABEL

Carton Label - One 200 mg Sterile Single-dose Vial - REZZAYO

PRINCIPAL DISPLAY PANEL

NDC 70842-240-01

Rx only

REZZAYO™
(rezafungin for injection)

200 mg per vial

*Vial contains rezafungin
200 mg (equivalent to 210 mg
of rezafungin acetate).

For intravenous Infusion Only

Must be reconstituted and
further diluted.

1 Sterile Single-Dose Vial

Discard unused portion.